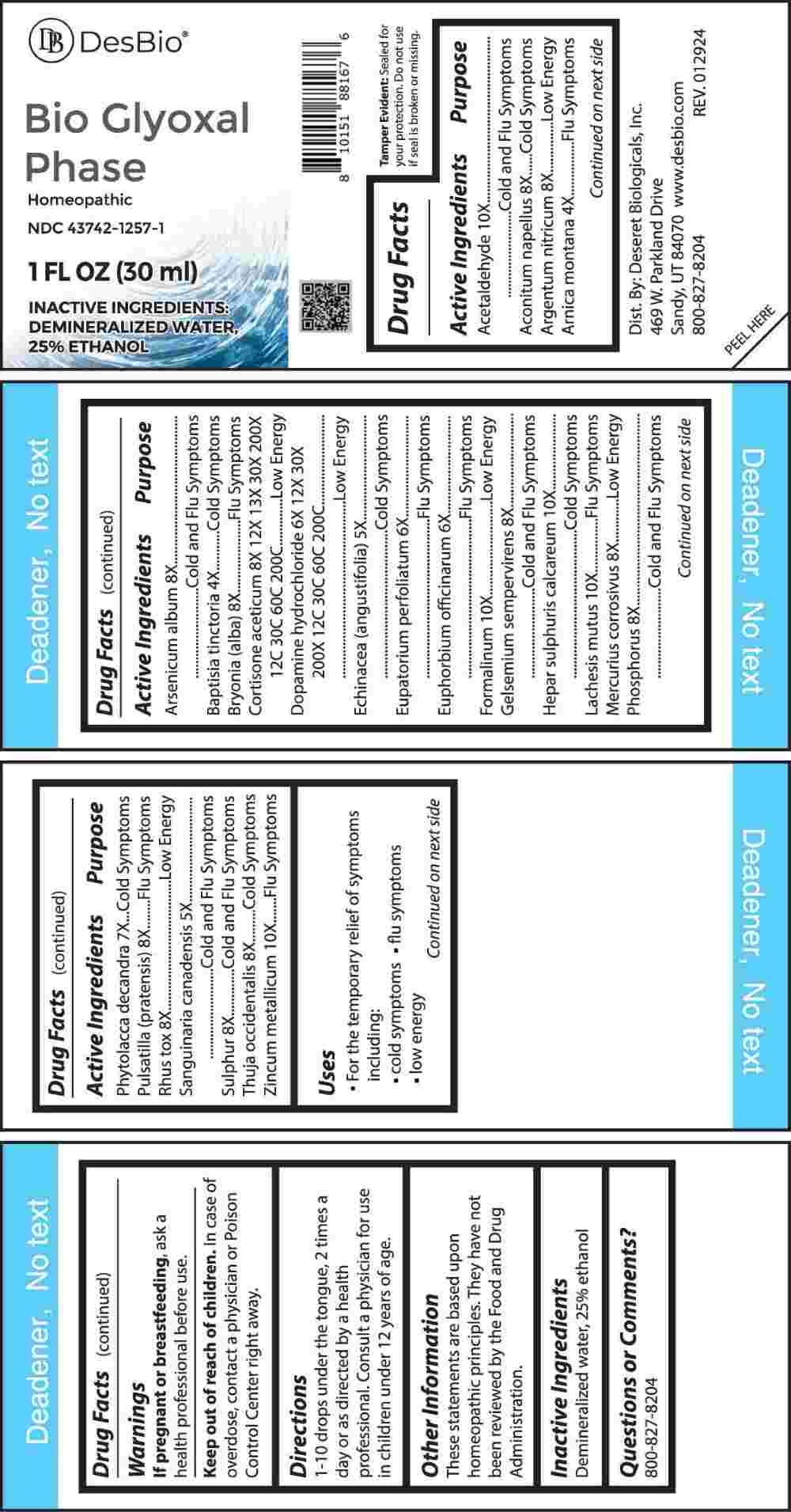 DRUG LABEL: Bio Glyoxal Phase
NDC: 43742-1257 | Form: LIQUID
Manufacturer: Deseret Biologicals, Inc.
Category: homeopathic | Type: HUMAN OTC DRUG LABEL
Date: 20240509

ACTIVE INGREDIENTS: ARNICA MONTANA WHOLE 4 [hp_X]/1 mL; BAPTISIA TINCTORIA ROOT 4 [hp_X]/1 mL; ECHINACEA ANGUSTIFOLIA WHOLE 5 [hp_X]/1 mL; SANGUINARIA CANADENSIS ROOT 5 [hp_X]/1 mL; EUPATORIUM PERFOLIATUM FLOWERING TOP 6 [hp_X]/1 mL; EUPHORBIA RESINIFERA RESIN 6 [hp_X]/1 mL; DOPAMINE HYDROCHLORIDE 6 [hp_X]/1 mL; PHYTOLACCA AMERICANA ROOT 7 [hp_X]/1 mL; ACONITUM NAPELLUS WHOLE 8 [hp_X]/1 mL; SILVER NITRATE 8 [hp_X]/1 mL; ARSENIC TRIOXIDE 8 [hp_X]/1 mL; BRYONIA ALBA ROOT 8 [hp_X]/1 mL; GELSEMIUM SEMPERVIRENS ROOT 8 [hp_X]/1 mL; MERCURIC CHLORIDE 8 [hp_X]/1 mL; PHOSPHORUS 8 [hp_X]/1 mL; PULSATILLA PRATENSIS WHOLE 8 [hp_X]/1 mL; TOXICODENDRON PUBESCENS LEAF 8 [hp_X]/1 mL; SULFUR 8 [hp_X]/1 mL; THUJA OCCIDENTALIS LEAFY TWIG 8 [hp_X]/1 mL; CORTISONE ACETATE 8 [hp_X]/1 mL; ACETALDEHYDE 10 [hp_X]/1 mL; FORMALDEHYDE 10 [hp_X]/1 mL; CALCIUM SULFIDE 10 [hp_X]/1 mL; LACHESIS MUTA VENOM 10 [hp_X]/1 mL; ZINC 10 [hp_X]/1 mL
INACTIVE INGREDIENTS: WATER; ALCOHOL

DRUG FACTS:

ACTIVE INGREDIENTS:

Acetaldehyde 10X, Aconitum Napellus 8X, Argentum Nitricum 8X, Arnica Montana 4X, Arsenicum Album 8X, Baptisia Tinctoria 4X, , Bryonia (Alba) 8X, Cortisone Aceticum 8X, 12X, 13X, 30X, 200X, 12C, 30C, 60C, 200C, Dopamine Hydrochloride 6X, 12X, 30X, 200X, 12C, 30C, 60C, 200C, Echinacea (Angustifolia) 5X, Eupatorium Perfoliatum 6X, Euphorbium Officinarum 6X, Formalinum 10X, Gelsemium Sempervirens 8X, Hepar Sulphuris Calcareum 10X, Lachesis Mutus 10X, Mercurius Corrosivus 8X, Phosphorus 8X, Phytolacca Decandra 7X, Pulsatilla (Pratensis) 8X, Rhus Tox 8X, Sanguinaria Canadensis 5X, Sulphur 8X, Thuja Occidentalis 8X, Zincum Metallicum 10X.

PURPOSE:

Acetaldehyde – Cold and Flu Symptoms, Aconitum Napellus – Cold Symptoms, Argentum Nitricum – Low Energy, Arnica Montana – Flu Symptoms, Arsenicum Album – Cold and Flu Symptoms, Baptisia Tinctoria – Cold Symptoms, Bryonia (Alba) – Flu Symptoms, Cortisone Aceticum – Low Energy, Dopamine Hydrochloride – Low Energy, Echinacea (Angustifolia) – Cold Symptoms, Eupatorium Perfoliatum – Flu Symptoms, Euphorbium Officinarum – Flu Symptoms, Formalinum – Low Energy, Gelsemium Sempervirens – Cold and Flu Symptoms, Hepar Sulphuris Calcareum – Cold Symptoms, Lachesis Mutus – Flu Symptoms, Mercurius Corrosivus – Low Energy, Phosphorus – Cold and Flu Symptoms, Phytolacca Decandra – Cold Symptoms, Pulsatilla (Pratensis) – Flu Symptoms, Rhus Tox – Low Energy, Sanguinaria Canadensis – Cold and Flu Symptoms, Sulphur – Cold and Flu Symptoms, Thuja Occidentalis – Cold Symptoms, Zincum Metallicum – Flu Symptoms

USES:

• For the temporary relief of symptoms including:

• cold symptoms • flu symptoms • low energy

These statements are based upon homeopathic principles. They have not been reviewed by the Food and Drug Administration.

WARNINGS:

If pregnant or breast-feeding, ask a health professional before use.

Keep out of reach of children. In case of overdose, contact a physician or Poison Control Center right away.

Tamper Evident: Sealed for your protection. Do not use if seal is broken or missing.

KEEP OUT OF REACH OF CHILDREN:

In case of overdose, contact physician or Poison Control Center right away.

DIRECTIONS:

1-10 drops under the tongue, 2 times a day or as directed by a health professional. Consult a physician for use in children under 12 years of age.

INACTIVE INGREDIENTS:

Demineralized water, 25% ethanol

QUESTIONS:

Dist. By: Deseret Biologicals, Inc.

469 W. Parkland Drive

Sandy, UT 84070

www.desbio.com

800-827-8204

PACKAGE LABEL DISPLAY:

Des Bio

Bio Glyoxal Phase

Homeopathic

NDC 43742-1257-1

1 FL OZ (30 ml)